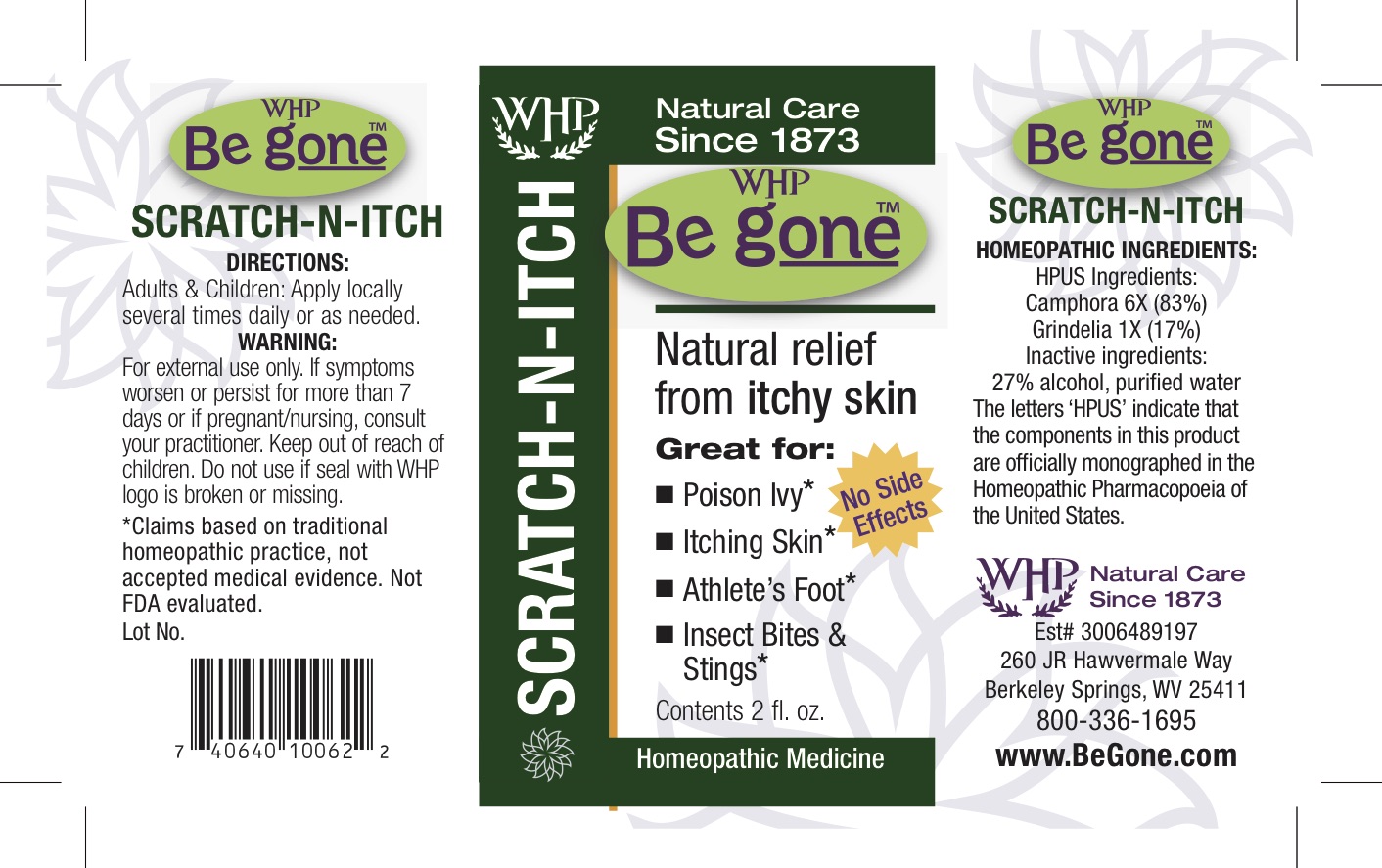 DRUG LABEL: Be gone SCRATCH-N-ITCH
NDC: 68428-727 | Form: SPRAY
Manufacturer: Washington Homeopathic Products
Category: homeopathic | Type: HUMAN OTC DRUG LABEL
Date: 20181113

ACTIVE INGREDIENTS: GRINDELIA SQUARROSA FLOWERING TOP 1 [hp_X]/60 mL; CAMPHOR (NATURAL) 1 [hp_X]/60 mL
INACTIVE INGREDIENTS: ALCOHOL; WATER O-15

DRUG FACTS

ACTIVE INGREDIENTS

GRINDELIA ø

CAMPHOR ø

USES

To relieve itchy skin.

KEEP OUT OF REACH OF CHILDREN

INDICATIONS

GRINDELIA Rash

CAMPHOR Coldness

STOP USE AND ASK DOCTOR

For external use only. If symptoms persist/worsen or if pregnant/nursing, consult your practitioner. Do not use if seal with WHP logo is broken or missing.

*Claims based on traditional homeopathic practice, not accepted medical evidence. Not FDA evaluated.

DIRECTIONS

Adults: Apply locally several times daily or as needed.

INACTIVE INGREDIENTS

20% Ethyl alcohol

USP water

PRINCIPAL DISPLAY PANEL

Be gone SCRATCH-N-ITCH Label